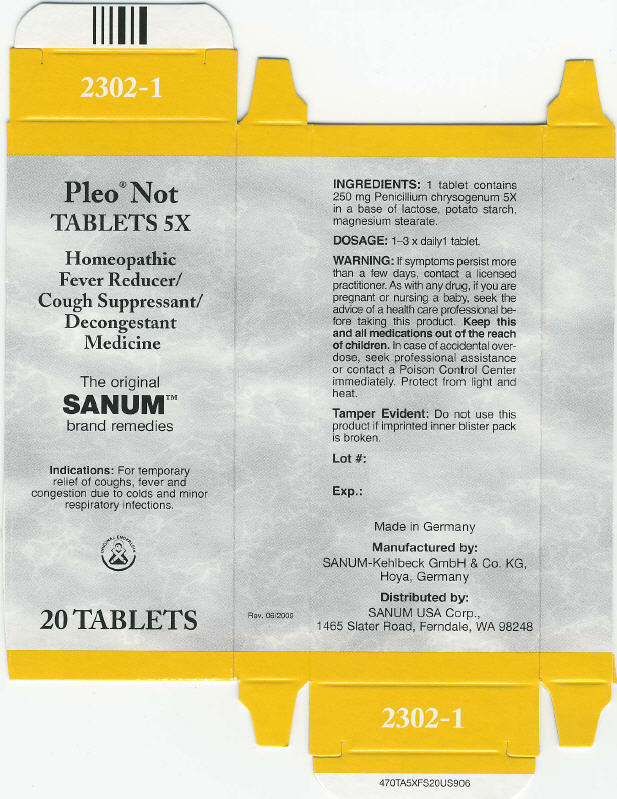 DRUG LABEL: Pleo Not
NDC: 60681-2302 | Form: TABLET
Manufacturer: Sanum Kehlbeck GmbH & Co. KG
Category: homeopathic | Type: HUMAN OTC DRUG LABEL
Date: 20091012

ACTIVE INGREDIENTS: penicillium chrysogenum var. chrysogenum 5 [HP_X]/1 1
INACTIVE INGREDIENTS: lactose; Starch, Potato; Magnesium Stearate

Pleo® Not
TABLETS 5X

Homeopathic Fever Reducer/Cough Suppressant/Decongestant Medicine

The original SANUM™ brand remedies

20 TABLETS

Indications

For temporary relief of coughs, fever and congestion due to colds and minor respiratory infections.

INGREDIENTS

1 tablet contains 250 mg Penicillium chrysogenum 5X in a base of lactose, potato starch, magnesium stearate.

DOSAGE

1–3 x daily1 tablet.

WARNING

If symptoms persist more than a few days, contact a licensed practitioner. As with any drug, if you are pregnant or nursing a baby, seek the advice of a health care professional before taking this product.

KEEP OUT OF REACH OF CHILDREN

Keep this and all medications out of the reach of children. In case of accidental overdose, seek professional assistance or contact a Poison Control Center immediately.

STORAGE AND HANDLING

Protect from light and heat.

Tamper Evident

Do not use this product if imprinted inner blister pack is broken.

Lot #:

Exp.:

Made in Germany

Manufactured by:
SANUM-Kehlbeck GmbH & Co. KG,
Hoya, Germany

Distributed by:
SANUM USA Corp.,
1465 Slater Road, Ferndale, WA 98248

Rev. 06/2009

PRINCIPAL DISPLAY PANEL - 20 Tablets Carton

Pleo® Not
TABLETS 5X

Homeopathic
Fever Reducer/
Cough Suppressant/
Decongestant
Medicine

The original
SANUM™
brand remedies

lndications: For temporary
relief of coughs, fever and
congestion due to colds and minor
respiratory infections.

ORIGINAL ENDERLEIN

20 TABLETS